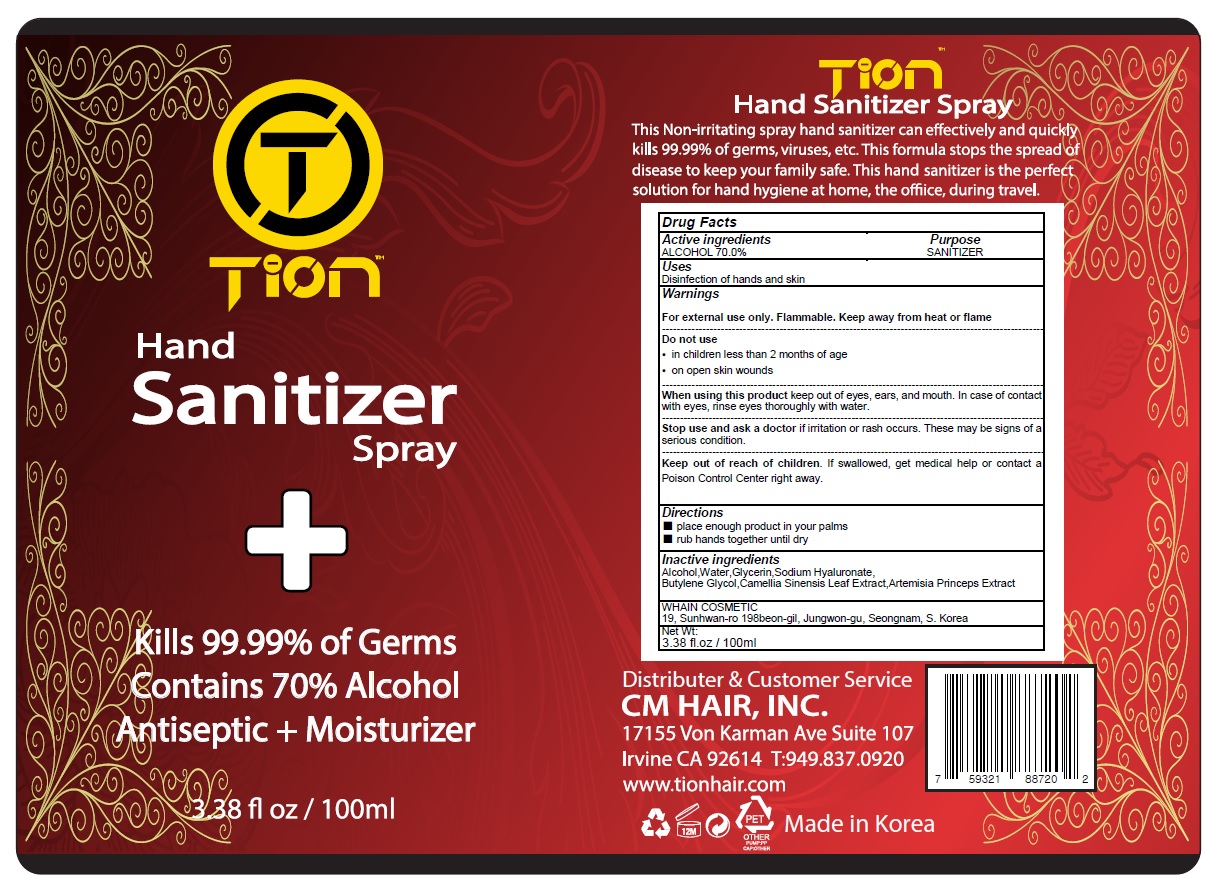 DRUG LABEL: TION HAND SANITIZER
NDC: 73823-050 | Form: SPRAY
Manufacturer: WHAIN COSMETIC
Category: otc | Type: HUMAN OTC DRUG LABEL
Date: 20200415

ACTIVE INGREDIENTS: ALCOHOL 350 g/100 mL
INACTIVE INGREDIENTS: Water; HYALURONATE SODIUM; Butylene Glycol; GREEN TEA LEAF

Active Ingredients

Active ingredients: ALCOHOL 70.0%

INACTIVE INGREDIENT

Inactive ingredients:

Water, Sodium Hyaluronate,Butylene Glycol,Camellia Sinensis Leaf Extract,Artemisia Princeps Extract

Purpose

Purpose: SANITIZER

Warnings

For external use only. Flammable. Keep away from heat or flame
--------------------------------------------------------------------------------------------------------
Do not use
• in children less than 2 months of age
• on open skin wounds
--------------------------------------------------------------------------------------------------------
When using this product keep out of eyes, ears, and mouth. In case of contact with eyes, rinse eyes thoroughly with water.
--------------------------------------------------------------------------------------------------------
Stop use and ask a doctor if irritation or rash occurs. These may be signs of a serious condition.

Keep out of reach of children. If swallowed, get medical help or contact a Poison Control Center right away.

Uses

Disinfection of hands and skin

Directions

■ place enough product in your palms
■ rub hands together until dry